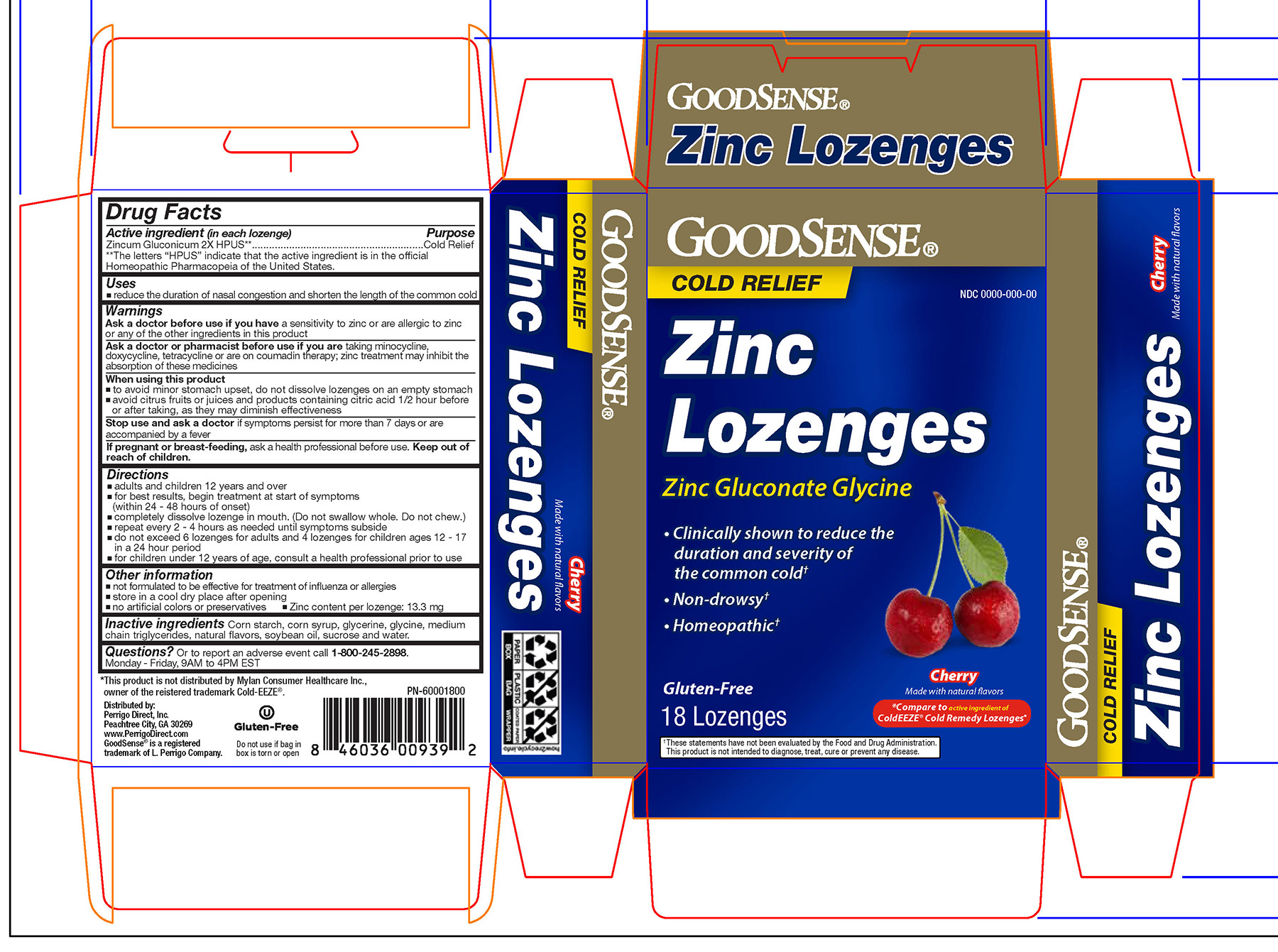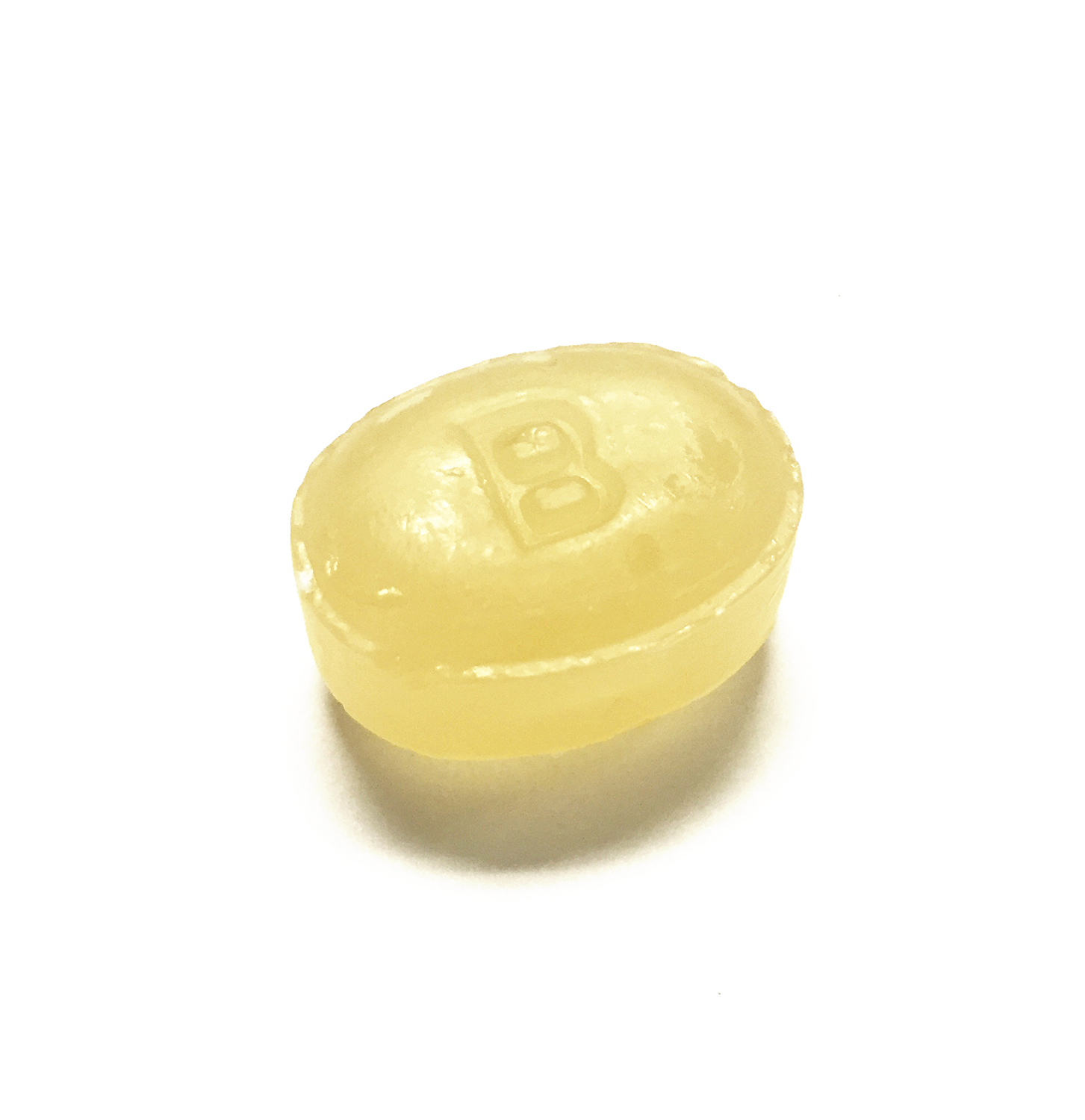 DRUG LABEL: GoodSense Cherry Zinc Lozenges
NDC: 75981-011 | Form: LOZENGE
Manufacturer: Geiss, Destin, & Dunn
Category: homeopathic | Type: HUMAN OTC DRUG LABEL
Date: 20210630

ACTIVE INGREDIENTS: ZINC GLUCONATE 2 [hp_X]/1 1
INACTIVE INGREDIENTS: WATER

Zincum Gluconicum 2X HPUS

Active ingredient (in each lozenge)

Zincum Gluconicum 2X HPUS**

**The letters "HPUS" indicate that the active ingredient is in the official Homeopathic Pharmacopeia of the United States.

Purpose

Cold Relief

Uses

- reduce the duration of nasal congestion and shorten the length of the common cold

Warnings

Ask a doctor before use if you have a sensitivity to zinc or are allergic to zinc or any of the other ingredients in this product.

Ask a doctor or pharmacist before use if you are taking minocycline, doxycycline, tetracycline, or are on coumadin therapy; zinc treatment may inhibit the absorption of these medicines.

When using this product

- to avoid minor stomach upset, do not dissolve lozenges on an empty stomach
- avoid citrus fruits and products containing citric acid 1/2 hour before or after taking, as they may diminish effectiveness.

Stop use and ask a doctor if symptoms persist for more than 7 days or are accompanied by a fever.

PREGNANCY OR BREAST FEEDING

If pregnant or breast-feeding, ask a health professional before use.

Keep out of reach of children.

Directions

- adults and children 12 years and over
- for best results, begin treatment at the start of symptoms (within 24 - 48 hours of onset)
- completely dissolve lozenge in mouth. (Do not swallow whole. Do not chew.)
- repeat every 2 - 4 hours as needed until symptoms subside
- do not exceed 6 lozenges for adults and 4 lozenges for children ages 12 - 17 in a 24 hour period
- for children under 12 years of age, consult a health professional prior to use

Other information

- not formulated to be effective for treatment of influenza or allergies
- store in a cool dry place after opening
- no artificial colors or preservatives
- Zinc content per lozenge: 13.3 mg

INACTIVE INGREDIENT

Inactive ingredients: Corn starch, corn syrup, glycerine, glycine, medium chain triglycerides, natural flavors, soybean oil, sucrose and water.

QUESTIONS

Questions? Or to report an adverse event call 1-800-245-2898. Monday - Friday, 9AM to 4PM EST